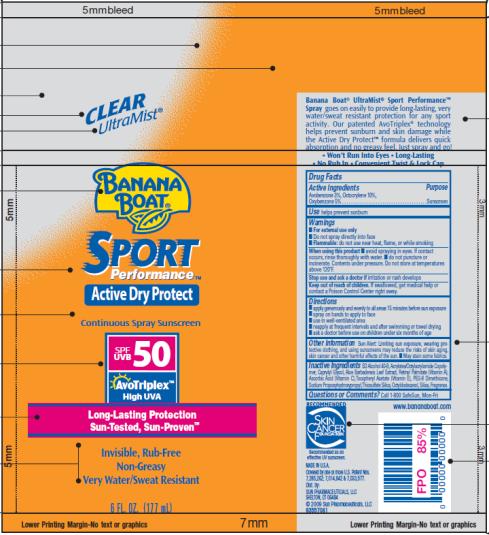 DRUG LABEL: Banana Boat Sport SPF 50
NDC: 17630-2032 | Form: SPRAY
Manufacturer: Accra-Pac, Inc.
Category: otc | Type: HUMAN OTC DRUG LABEL
Date: 20100327

ACTIVE INGREDIENTS: AVOBENZONE 0.03 mL/1 mL; OCTOCRYLENE 0.10 mL/1 mL; OXYBENZONE 0.05 mL/1 mL
INACTIVE INGREDIENTS: CAPRYLYL GLYCOL; ALOE VERA LEAF; VITAMIN A PALMITATE; ASCORBIC ACID; .ALPHA.-TOCOPHEROL ACETATE, D-; OCTYLDODECANOL; SILICON DIOXIDE

Banana Boat Sport SPF 50

Drug Facts

Active Ingredients

Avobenzone 0.03mL / 1mL

Octocrylene 0.10mL / 1mL

Oxybenzone 0.05mL / 1mL

Purpose

Sunscreen

Use

helps prevent sunburn

Warnings

- For external use only
- Do not spray directly into face
- Flammable: do not use near heat, flame, or while smoking

When using this product

- avoid spraying in eyes. If contact occurs, rinse thoroughly with water.
- do not puncture or incinerate. Contents under pressure. Do not store at temperatures above 120°F.

Stop use and ask a doctor if

irritation or rash develops

Keep out of reach of children.

If swallowed, get medical help or contact a Poison Control Center right away.

Directions

- apply generously and evenly to all areas 15 minutes before sun exposure
- spray on hands to apply to face
- use in well-ventilated area
- reapply at frequent intervals and after swimming or towel drying
- ask a doctor before use on children under six months of age

Other Information

Sun Alert: Limiting sun exposure, wearing protective clothing, and using sunscreens may reduce the risks of skin aging, skin cancer and other harmful effects of the sun. _ May stain some fabrics.

Inactive Ingredients

SD Alcohol 40-B, Acrylates/Octylacrylamide Copolymer, Caprylyl Glycol, Aloe Barbadensis Leaf Extract, Retinyl Palmitate (Vitamin A), Ascorbic Acid (Vitamin C), Tocopheryl Acetate (Vitamin E), PEG-8 Dimethicone, Sodium Propoxyhydroxypropyl, Thiosulfate Silica, Octyldodecanol, Silica, Fragrance.

Questions or Comments?

Call 1-800 SafeSun, Mon-Fri

MADE IN U.S.A.
Dist. by:
SUN PHARMACEUTICALS, LLC
SHELTON, CT 06484
© 2009 Sun Pharmaceuticals, LLC

PRINCIPAL DISPLAY PANEL

CLEAR
UltraMist®
BANANA
BOAT®
SPORT
PerformanceTM
Active Dry Protect
Continuous Spray Sunscreen
SPF/UVB 50
AvoTriplexTM
High UVA
Long-Lasting Protection
Sun-Tested, Sun-ProvenTM
Invisible, Rub-Free
Non-Greasy
Very Water/Sweat Resistant
6 FL. OZ. (177 mL)